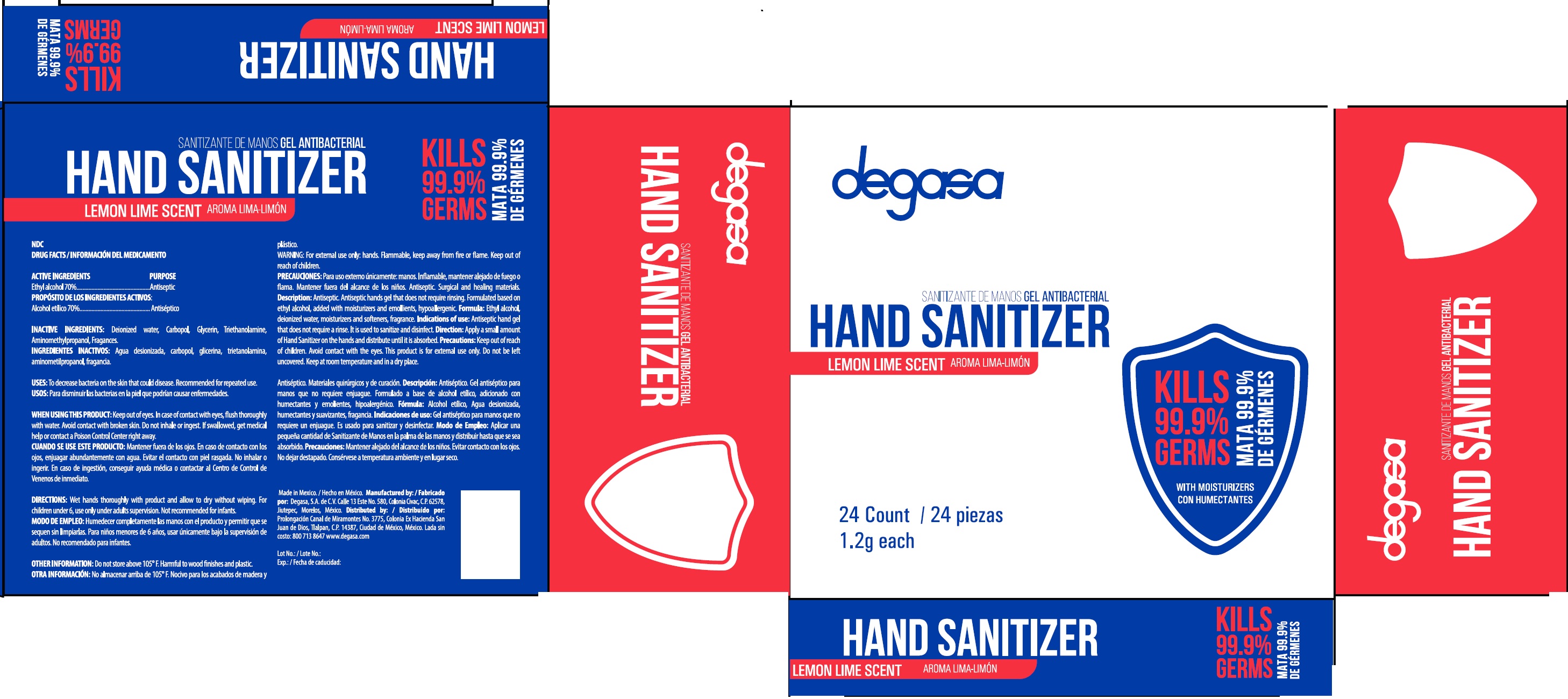 DRUG LABEL: Hand Sanitizer
NDC: 67326-400 | Form: CLOTH
Manufacturer: Degasa, S.A. de C.V.
Category: otc | Type: HUMAN OTC DRUG LABEL
Date: 20231105

ACTIVE INGREDIENTS: ALCOHOL 0.7 g/1 g
INACTIVE INGREDIENTS: WATER; CARBOMER HOMOPOLYMER, UNSPECIFIED TYPE; GLYCERIN; TROLAMINE; AMINOMETHYLPROPANOL

Hand Sanitizer

ACTIVE INGREDIENTS

Ethyl alcohol 70%

PURPOSE

Antiseptic

INACTIVE INGREDIENTS:

Deionized water, Carbopol, Glycerin, Triethanolamine, Aminomethylpropanol, Fragances.

USES:

To decrease bacteria on the skin that could disease. Recommended for repeated use.

WARNINGS

WHEN USING THIS PRODUCT:

Keep out of eyes. In case of contact with eyes, flush thoroughly with water. Avoid contact with broken skin. Do not inhale or ingest.

KEEP OUT OF REACH OF CHILDREN

If swallowed, get medical help or contact a Poison Control Center right away.

DIRECTIONS:

Wet hands thoroughly with product and allow to dry without wiping. For children under6, use only under adults supervision. Not recommended for infants.

OTHER INFORMATION:

Do not store above 105°F.Harmful to wood finished and plastic.